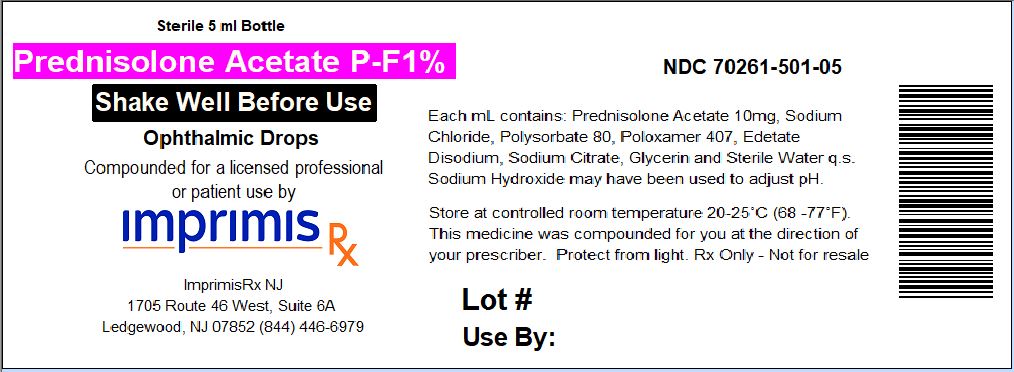 DRUG LABEL: Prednisolone Acetate PF
NDC: 70261-501 | Form: SUSPENSION/ DROPS
Manufacturer: ImprimisRx NJ
Category: prescription | Type: HUMAN PRESCRIPTION DRUG LABEL
Date: 20180508

ACTIVE INGREDIENTS: PREDNISOLONE ACETATE 10 mg/1 mL

STORAGE AND HANDLING

Store at 20° to 25° C (68° to 77° F)